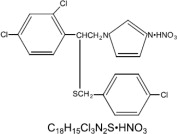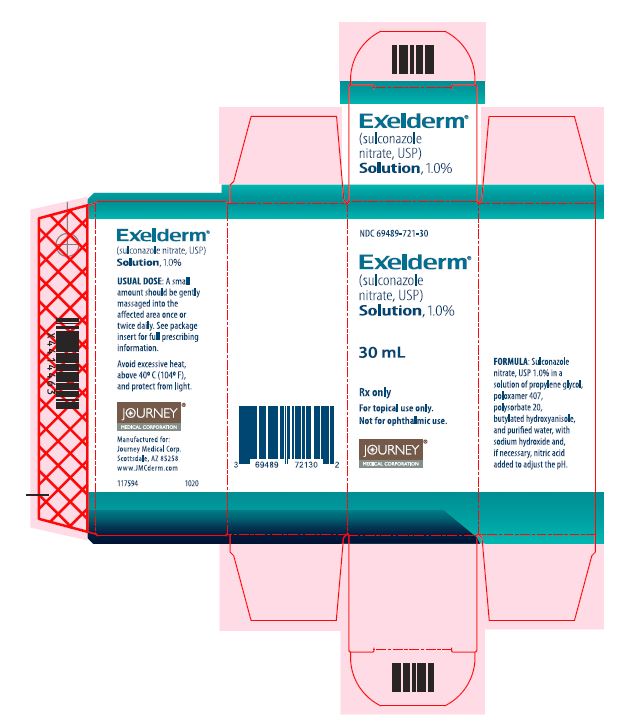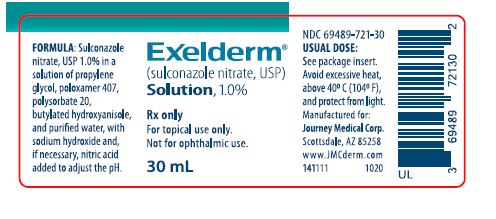 DRUG LABEL: Exelderm
NDC: 69489-721 | Form: SOLUTION
Manufacturer: Journey Medical Corporation
Category: prescription | Type: HUMAN PRESCRIPTION DRUG LABEL
Date: 20221108

ACTIVE INGREDIENTS: Sulconazole Nitrate 10 mg/1 mL
INACTIVE INGREDIENTS: Propylene glycol; Poloxamer 407; Polysorbate 20; Butylated Hydroxyanisole; Water; Sodium hydroxide; Nitric acid

Exelderm®

(sulconazole nitrate, USP)
Solution, 1.0%

Rx only

For topical use only. Not for ophthalmic use.

DESCRIPTION

EXELDERM (sulconazole nitrate, USP) SOLUTION, 1.0% is a broad-spectrum antifungal agent intended for topical application. Sulconazole nitrate, USP, the active ingredient in EXELDERM SOLUTION, is an imidazole derivative with antifungal and antiyeast activity. Its chemical name is (±)-1-[2,4-dichloro-β-[(p-chlorobenzyl)-thio]-phenethyl] imidazole mononitrate and it has the following chemical structure:

Sulconazole nitrate, USP is a white to off-white crystalline powder with a molecular weight of 460.77. It is freely soluble in pyridine; slightly soluble in ethanol, acetone, and chloroform; and very slightly soluble in water. It has a melting point of about 130°C.

EXELDERM SOLUTION contains sulconazole nitrate, USP 10 mg/mL in a solution of propylene glycol, poloxamer 407, polysorbate 20, butylated hydroxyanisole, and purified water, with sodium hydroxide and, if necessary, nitric acid added to adjust the pH.

CLINICAL PHARMACOLOGY

Sulconazole nitrate is an imidazole derivative that inhibits the growth of the common pathogenic dermatophytes including Trichophyton rubrum, Trichophyton mentagrophytes, Epidermophyton floccosum, and Microsporum canis. It also inhibits the organism responsible for tinea versicolor, Malassezia furfur, and certain gram-positive bacteria.

A maximization test with sulconazole nitrate solution showed no evidence of irritation or contact sensitization.

INDICATIONS AND USAGE

EXELDERM (sulconazole nitrate, USP) SOLUTION, 1.0% is a broad-spectrum antifungal agent indicated for the treatment of tinea cruris and tinea corporis caused by Trichophyton rubrum, Trichophyton mentagrophytes, Epidermophyton floccosum, and Microsporum canis; and for the treatment of tinea versicolor. Effectiveness has not been proven in tinea pedis (athlete's foot).

Symptomatic relief usually occurs within a few days after starting EXELDERM SOLUTION and clinical improvement usually occurs within one week.

CONTRAINDICATIONS

EXELDERM (sulconazole nitrate, USP) SOLUTION, 1.0% is contraindicated in patients who have a history of hypersensitivity to any of the ingredients.

PRECAUTIONS

General

EXELDERM (sulconazole nitrate, USP) SOLUTION, 1.0% is for external use only. Avoid contact with the eyes. If irritation develops, the solution should be discontinued and appropriate therapy instituted.

Information for Patients

Patients should be told to use EXELDERM SOLUTION as directed by the physician, to use it externally only, and to avoid contact with the eyes.

Carcinogenesis, Mutagenesis, Impairment of Fertility

Long-term animal studies to determine carcinogenic potential have not been performed. In vitro studies have shown no mutagenic activity.

Pregnancy

Sulconazole nitrate has been shown to be embryotoxic in rats when given in doses 125 times the human dose (in mg/kg). The drug at this dose given orally to rats also resulted in prolonged gestation and dystocia. Several females died during the perinatal period, most likely due to labor complications. Sulconazole nitrate was not teratogenic in rats or rabbits at oral doses of 50 mg/kg/day.

There are no adequate and well-controlled studies in pregnant women. Sulconazole nitrate should be used during pregnancy only if the potential benefit justifies the potential risk to the fetus.

Nursing Mothers

It is not known whether this drug is excreted in human milk. Because many drugs are excreted in human milk, caution should be exercised when sulconazole nitrate is administered to a nursing woman.

Pediatric Use

Safety and effectiveness in children have not been established.

Geriatric Use

Clinical studies of EXELDERM SOLUTION, 1.0%, did not include sufficient numbers of patients aged 65 years and over to determine whether they respond differently than younger patients. Other reported clinical experience has not identified differences in responses between elderly and younger patients.

ADVERSE REACTIONS

There were no systemic effects and only infrequent cutaneous adverse reactions in 370 patients treated with sulconazole nitrate solution in controlled clinical trials. Approximately 1% of these patients reported itching and 1% burning or stinging. These complaints did not usually interfere with treatment.

DOSAGE AND ADMINISTRATION

A small amount of solution should be gently massaged into the affected and surrounding skin areas once or twice daily.

Symptomatic relief usually occurs within a few days after starting EXELDERM (sulconazole nitrate) SOLUTION, 1.0%, and clinical improvement usually occurs within 1 week. To reduce the possibility of recurrence, tinea cruris, tinea corporis, and tinea versicolor should be treated for 3 weeks.

If significant clinical improvement is not seen after 4 weeks of treatment, an alternate diagnosis should be considered.

HOW SUPPLIED

EXELDERM (sulconazole nitrate, USP) SOLUTION, 1.0% is a clear, slightly viscous, colorless to slightly yellow liquid with a slight characteristic odor. It is supplied as follows:

30 mL plastic bottle – NDC 69489-721-30

Avoid excessive heat, above 40° C (104° F), and protect from light.

To report SUSPECTED ADVERSE REACTIONS, contact the FDA at 1-800-FDA-1088 or www.fda.gov/medwatch.

JOURNEY®
MEDICAL CORPORATION

Manufactured for:
Journey Medical Corp.
Scottsdale, AZ 85258
www.JMCderm.com

141112 Revised March 2021

Principal Display Panel – 30 mL Bottle Label

NDC 69489-721-30

Exelderm®

(sulconazole
nitrate, USP)
Solution, 1.0%

30 mL

Rx only

For topical use only.

Not for ophthalmic use.

JOURNEY

MEDICAL CORPORATION

Principal Display Panel – 30 mL Bottle Label

Exelderm® NDC 69489-721-30

(sulconazole nitrate, USP)
Solution, 1.0%

Rx only

For topical use only.

Not for ophthalmic use.

30 mL